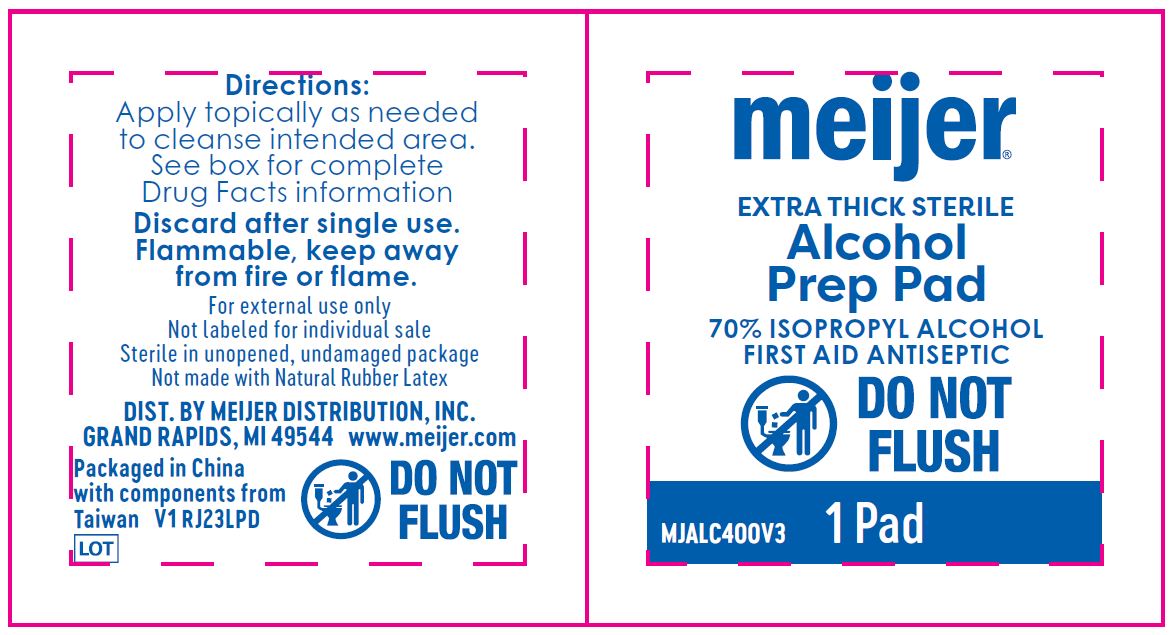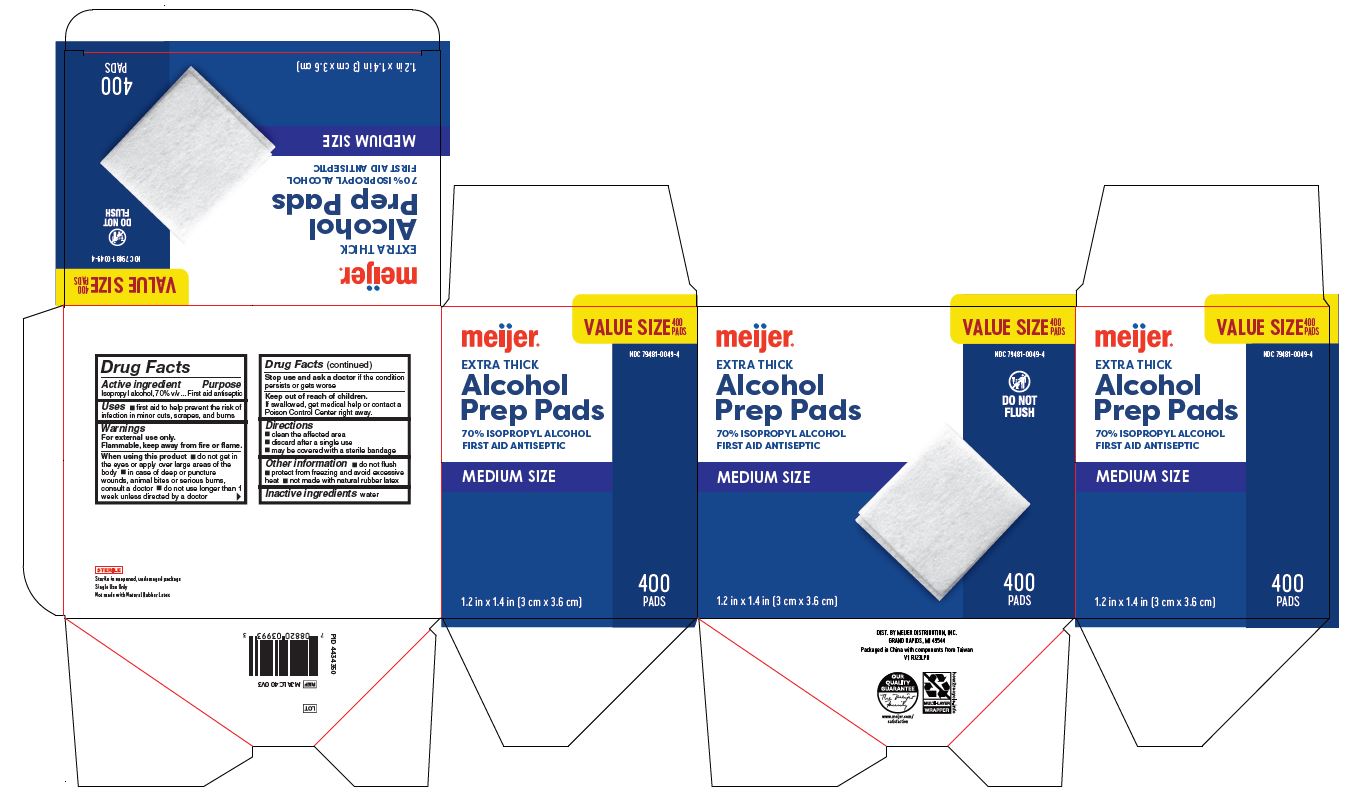 DRUG LABEL: Meijer
NDC: 79481-0049 | Form: SWAB
Manufacturer: Meijer Distribution Inc
Category: otc | Type: HUMAN OTC DRUG LABEL
Date: 20250103

ACTIVE INGREDIENTS: ISOPROPYL ALCOHOL 70 mL/100 mL
INACTIVE INGREDIENTS: WATER

79481-0049 Meijer Alcohol Prep Pad

Active ingredient

Isopropyl alcohol 70% v/v

Purpose

First aid antiseptic

Uses

- first aid antiseptic to help prevent the risk of infection in minor cuts, scrapes and burns

Warnings

For external use only.

Flammable, keep away from fire or flame.

When using this product

- do not get in the eyes or apply over large areas of the body
- in case of deep or puncture wounds, animal bites or serious burns, consult a doctor
- do not use longer than 1 week unless directed by a doctor

Stop use and ask a doctor if

- the condition persists or gets worse

Keep out of reach of children.

If swallowed, get medical help or contact a Poison Control Center right away.

Directions

- clean the affected are
- discard after single use
- may be covered with a sterile bandage

Other information

- do not flush
- protect from freezing and avoid excessive heat
- not made with natural rubber latex

Inactive ingredient

water

Manufacturing Information

Distributed by:

Meijer Distribution, Inc.

2929 Walker Ave NW, Grand Rapids, MI 49544 USA

Packaged in China with components from Taiwan

www.meijer.com

REF: MJALC400V3

V1 RJ23LPD